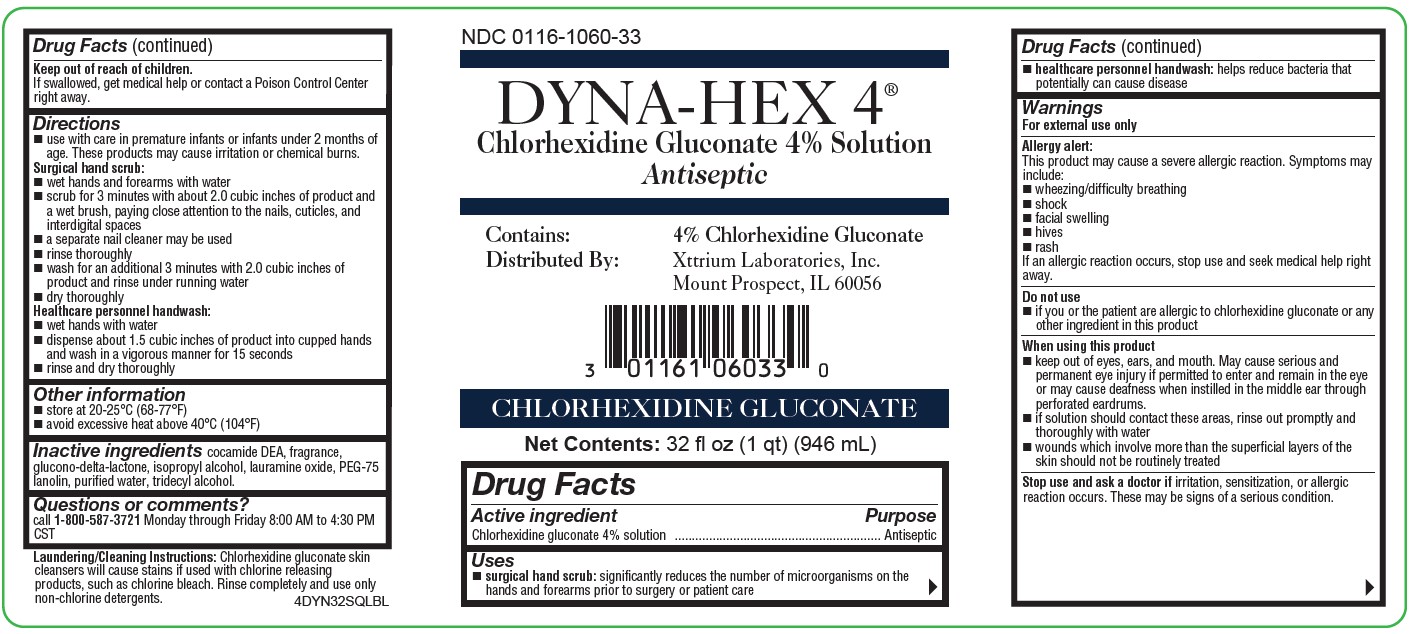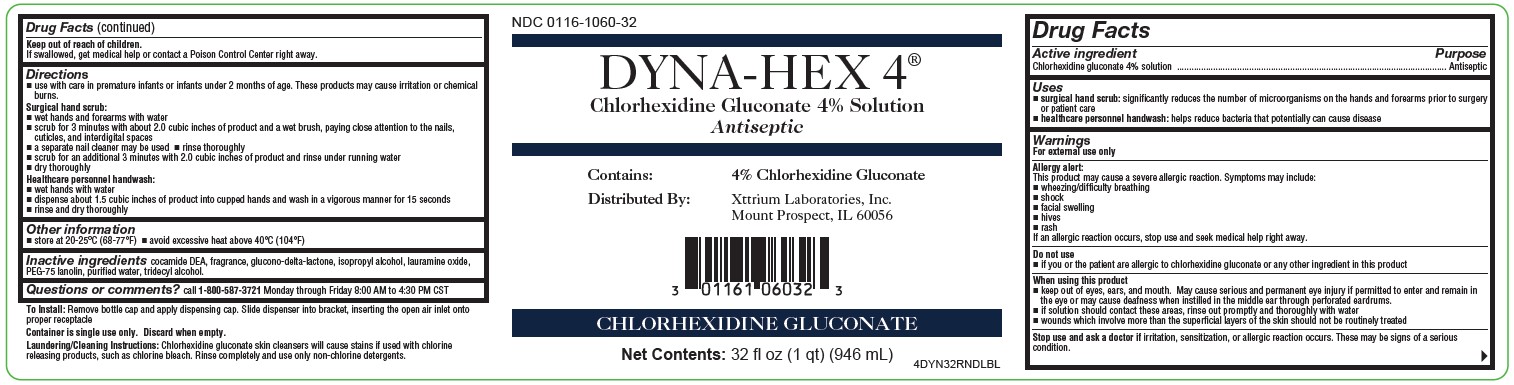 DRUG LABEL: Dyna-Hex 4
NDC: 0116-1060 | Form: LIQUID
Manufacturer: Xttrium Laboratories, Inc.
Category: otc | Type: HUMAN OTC DRUG LABEL
Date: 20250430

ACTIVE INGREDIENTS: CHLORHEXIDINE GLUCONATE 4 g/100 mL
INACTIVE INGREDIENTS: PEG-75 LANOLIN; ISOPROPYL ALCOHOL; GLUCONOLACTONE; WATER; LAURAMINE OXIDE; TRIDECYL ALCOHOL; COCO DIETHANOLAMIDE

Dyna-Hex 32oz Round & Sqaure Bottle

Active ingredient

Chlorhexidine gluconate 4% solution

Purpose

Antiseptic

Uses

 surgical hand scrub: significantly reduces the number of microorganisms on the hands and forearms prior to surgery or patient care
 healthcare personnel handwash: helps reduce bacteria that potentially can cause disease

Warnings

For external use only

Allergy alert:
This product may cause a severe allergic reaction. Symptoms may include:

 wheezing/difficulty breathing
 shock
 facial swelling
 hives
 rash
If an allergic reaction occurs, stop use and seek medical help right away.

Do not use

- if you or the patient are allergic to chlorhexidine gluconate or any other ingredient in this product

When using this product

 keep out of eyes, ears, and mouth. May cause serious and permanent eye injury if permitted to enter and remain in the eye or may cause deafness when instilled in the middle ear through perforated eardrums.
 if solution should contact these areas, rinse out promptly and thoroughly with water
 wounds which involve more than the superficial layers of the skin should not be routinely treated

Stop use and ask a doctor if

irritation, sensitization, or allergic reaction occurs. These may be signs of a serious condition.

Keep out of reach of children.

If swallowed, get medical help or contact a Poison Control Center right away.

Directions

 use with care in premature infants or infants under 2 months of age. These products may cause irritation or chemical burns.
Surgical hand scrub:
 wet hands and forearms with water
 scrub for 3 minutes with about 2.0 cubic inches of product and a wet brush, paying close attention to the nails, cuticles, and interdigital spaces
 a separate nail cleaner may be used  rinse thoroughly
 scrub for an additional 3 minutes with 2.0 cubic inches of product and rinse under running water
 dry thoroughly
Healthcare personnel handwash:
 wet hands with water
 dispense about 1.5 cubic inches of product into cupped hands and wash in a vigorous manner for 15 seconds
 rinse and dry thoroughly

Other Information

 store at 20-25°C (68-77°F)  avoid excessive heat above 40°C (104°F)

INACTIVE INGREDIENT

cocamide DEA, fragrance, glucono-delta-lactone, isopropyl alcohol, lauramine oxide, PEG-75 lanolin, purified water, tridecyl alcohol.

Questions or comments?

call 1-800-587-3721 Monday through Friday 8:00 AM to 4:30 PM CST

OTHER SAFETY INFORMATION

To Install: Remove bottle cap and apply dispensing cap. Slide dispenser into bracket, inserting the open air inlet onto proper receptacle
Container is single use only. Discard when empty.

Laundering/Cleaning Instructions:

Chlorhexidine gluconate skin cleansers will cause stains if used with chlorine releasing products, such as chlorine bleach. Rinse completely and use only non-chlorine detergents.

Principle Display Panel

NDC 0116-1060-32
DYNA-HEX 4®
Chlorhexidine Gluconate 4% Solution
Antiseptic
Contains: 4% Chlorhexidine Gluconate
Distributed By: Xttrium Laboratories, Inc. Mount Prospect, IL 60056
CHLORHEXIDINE GLUCONATE
Net Contents: 32 fl oz (1 qt) (946 mL)
4DYN32RNDLBL

NDC 0116-1060-33
DYNA-HEX 4®
Chlorhexidine Gluconate 4% Solution
Antiseptic
Contains: 4% Chlorhexidine Gluconate
Distributed By: Xttrium Laboratories, Inc. Mount Prospect, IL 60056
CHLORHEXIDINE GLUCONATE
Net Contents: 32 fl oz (1 qt) (946 mL)

4DYN32SQLBL